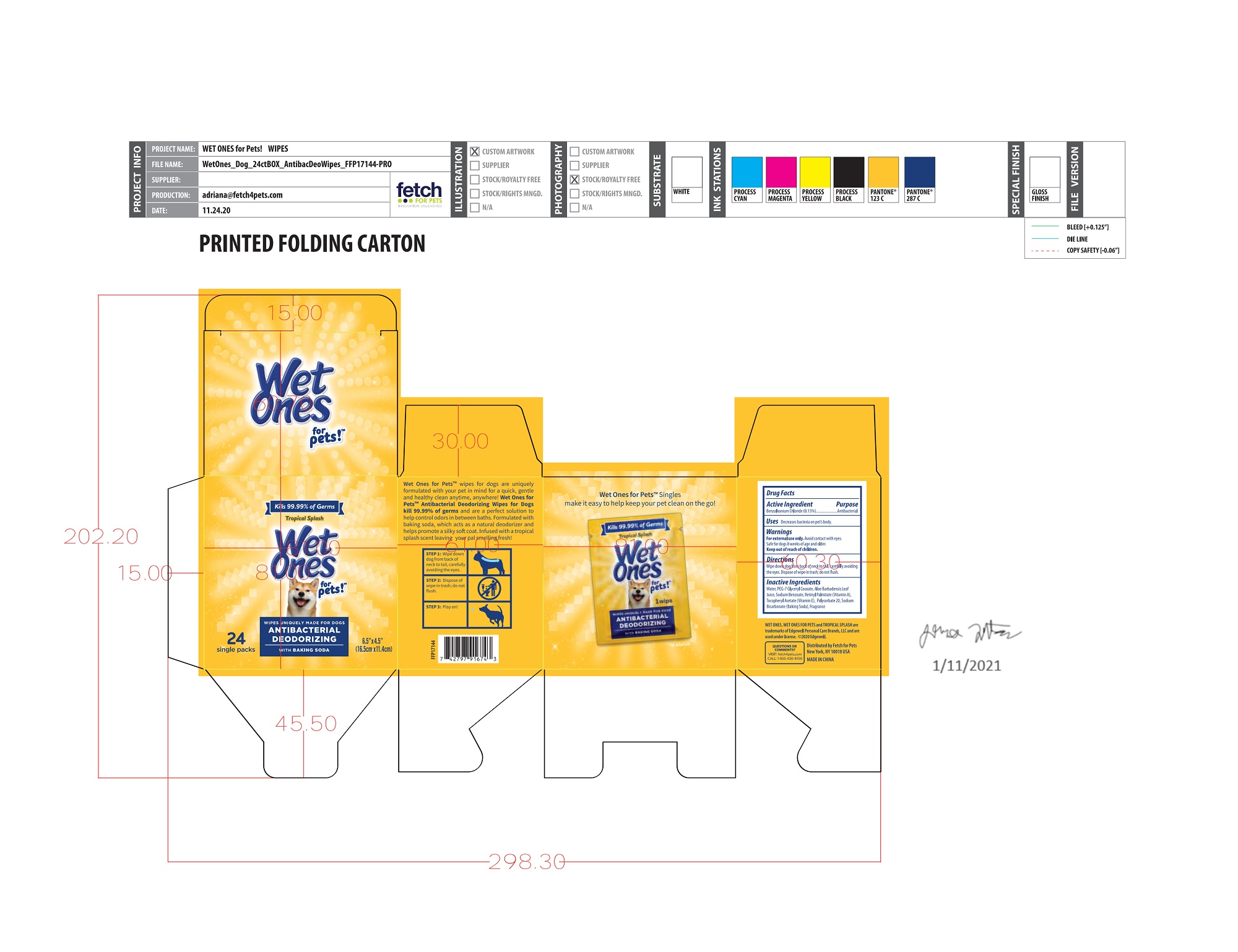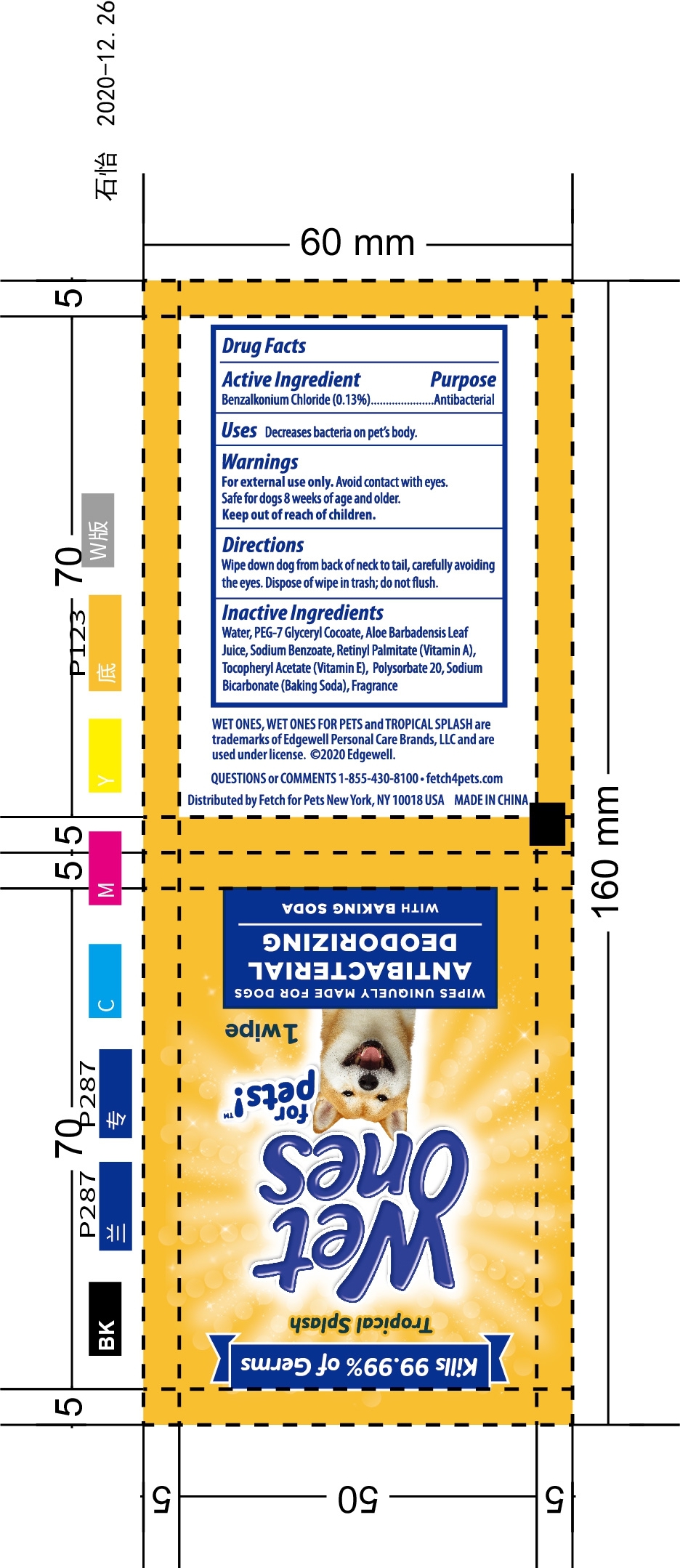 DRUG LABEL: ANTIBACTERIAL DEODORIZING WIPES
NDC: 77720-022 | Form: CLOTH
Manufacturer: Skaffles Group Limited Liability Company
Category: animal | Type: OTC ANIMAL DRUG LABEL
Date: 20210119

ACTIVE INGREDIENTS: BENZALKONIUM CHLORIDE 0.13 g/100 g
INACTIVE INGREDIENTS: WATER; VITAMIN A PALMITATE; .ALPHA.-TOCOPHEROL ACETATE; ALOE VERA LEAF; POLYSORBATE 20; SODIUM BICARBONATE; SODIUM BENZOATE; PEG-7 GLYCERYL COCOATE

Active Ingredient

Benzalkonium Chloride 0.13%

USE

Decreases Bacteria on pets body.

Warning

For external use only.

Avoid Contact with eyes. Safe for dogs 8 weeks of age and older.

Keep out of reach of children.

Directions

Wipe down dog from back of neck to tail,carefully avoiding the eyes.

didpose of wipe in trash ,do not flush

Inactive ingredients

Water, PEG-7Glyceryl Cocoate,Aloe Barbadensis LeafJuice, Sodium Benzoate,Retinyl Palmitate (Vitamin A),Tocopheryl Acetate (Vitamin E), Polysorbate 20,SodiumBicarbonate(Baking Soda), Fragrance